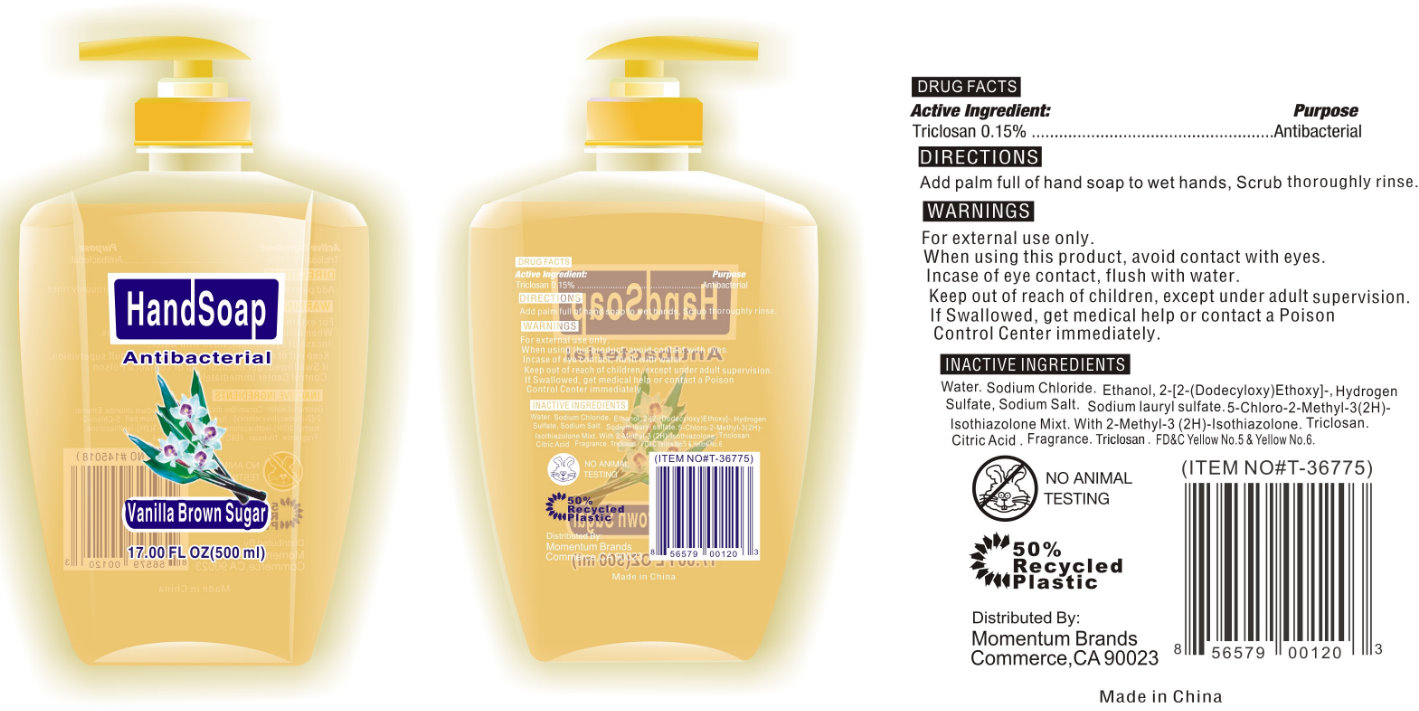 DRUG LABEL: Antibacterial Hand -Vanilla Brown Sugar
NDC: 42302-011 | Form: SOAP
Manufacturer: Lonkey Overseas Inc.
Category: otc | Type: HUMAN OTC DRUG LABEL
Date: 20120125

ACTIVE INGREDIENTS: TRICLOSAN 0.15 mL/100 mL
INACTIVE INGREDIENTS: WATER; SODIUM CHLORIDE; SODIUM LAURYL SULFATE; DIMETHYL LAURAMINE; SODIUM SULFATE; SODIUM C14 OLEFIN SULFONATE; TRICLOSAN; CITRIC ACID MONOHYDRATE; METHYLCHLOROISOTHIAZOLINONE; GLYCOL DISTEARATE; FD&C YELLOW NO. 5; FD&C YELLOW NO. 6

Antibacterial Hand Soap Vanilla Brown Sugar

Active Ingredient:

Triclosan 0.15%

Purpose

Antibacterial

Uses:

For handwashing to decrease bacteria on the skin

Warnings

For external use only.

When using this product, avoid contact with eyes.

In case of eye contact, flush with water.

Keep out of reach of children, except under adult supervision.

If swallowed, get medical help or contact a Poison Control Center immediately.

Directions

Add palm full of hand soap to wet hands, Scrub thoroughly rinse.

Inactive Ingredients

Distilled Water, Sodium CHloride, Sodium Lauryl Ether Sulfate, N,N-dimethyldodecylamine-N-oxide sol, Lauril Sulfato de Sodio, Sodio C14-16 Olefina Sulfonato, Triclosan, Citric Acid, Mezcla de 5-cloro-2-metil-3(2H)-isotiazolon.2-Metil-2Hisotiazol-3-on, Fragrance, FD C Yellow No.5 and Yellow No.6.

All Rights Reserved

Distributed By:

LONKEY OVERSEAS INCORPORATION

MADE IN CHINA

Antibacterial Hand Soap - Vanilla Brown Sugar 17oz/500ml (42302-011-00

Antibacterial

Hand Soap

Vanilla

Brown Sugar

17.00FL OZ (500ml)